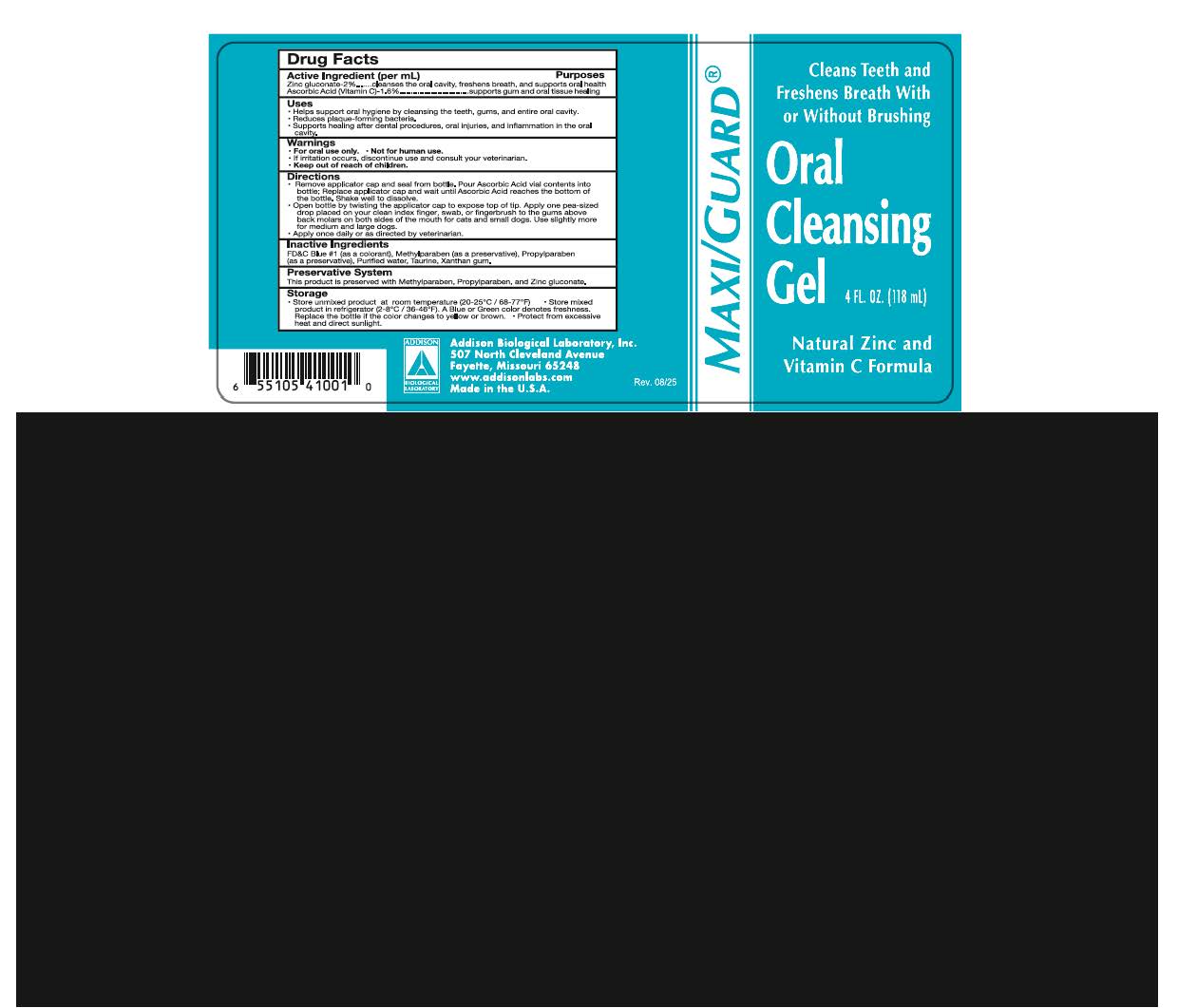 DRUG LABEL: Maxi/Guard Oral Cleansing Gel
NDC: 86045-9100 | Form: GEL
Manufacturer: Addison Biological Laboratory, Inc.
Category: animal | Type: OTC ANIMAL DRUG LABEL
Date: 20251212

ACTIVE INGREDIENTS: ZINC GLUCONATE 0.022 g/1 mL; ASCORBIC ACID 0.016 g/1 mL
INACTIVE INGREDIENTS: WATER; TAURINE; XANTHAN GUM; METHYLPARABEN; PROPYLPARABEN; FD&C BLUE NO. 1

Maxi/Guard Oral Cleansing Gel

INDICATIONS AND USAGE

BENEFITS: Cleanses Teeth and freshens the breath With or Without Brushing

ACTIVE INGREDIENT

Active Ingredient (per mL) Purposes

Zinc gluconate- 2%.......cleanses the oral cavity, freshens breath, and supports oral health

Ascorbic Acid (Vitamin C)-1.6%..............................supports gum and oral tissue healing

USES

- Helps support oral hygiene by cleansing the teeth, gums, and entire oral cavity.
- Reduces plaque-forming bacteria.
- Supports healing after dental procedures, oral injuries, and inflammation in the oral cavity.

WARNINGS

- For oral use only.
- Not for human use.
- If irritation occurs, discontinue use and consult your veterinarian.
- Keep out of reach of children.

DIRECTIONS

- Remove applicator cap and seal from bottle.Pour Ascorbic Acid vial contents into bottle; Replace applicator cap and wait until Ascorbic Acid reaches the bottom of bottle.Shake well to dissolve.
- Open bottle by twisting the applicator cap to expose top of tip. Apply one pea-sized drop placed on your clean index finger,swab, or fingerbrush to the gums above back molars on both sides of the mouth for cats and small dogs.Use slighty more for medium and large dogs.
- Apply once daily or as directed by veterinarian.

INACTIVE INGREDIENT

INGREDIENTS: F.D.&C. Blue No.1 (as a colorant),Methylparaben (as a preservative),Propylparaben (as a preservative),Purified Water, Taurine, Xanthan Gum.

PRESERVATIVE SYSTEM

This product is preserved with Methylparaben, Propylparaben, and Zinc gluconate.

STORAGE

- Store unmixed product at room temperature (20-25°C/ 68-77°F)
- Store mixed product in refrigerator (2-8°C/36-46°F).A Blue or Green color denotes freshness.Replace the bottle if the color changes to yellow or brown.
- Protect from excessive heat and direct sunlight.

Addison Biological Laboratory, Inc.

507 North Cleveland Avenue
Fayette, Missouri 65248
www.addisonlabs.com
Made in the U.S.A.

Rev. 08/25

LABEL with DRUG FACTS

Maxi/Guard®

Cleans Teeth and

Freshens Breath With

or Without Brushing

Oral Cleansing Gel
4FL. OZ. (118mL)
Natural Zinc and
Vitamin C formula

Drug Facts

Active Ingredient (per mL) Purposes

Zinc gluconate- 2%.......cleanses the oral cavity, freshens breath, and supports oral health

Ascorbic Acid (Vitamin C)-1.6%..............................supports gum and oral tissue healing

Uses

- Helps support oral hygiene by cleansing the teeth, gums, and entire oral cavity.
- Reduces plaque-forming bacteria.
- Supports healing after dental procedures, oral injuries, and inflammation in the oral cavity.

Warnings

- For oral use only.
- Not for human use.
- If irritation occurs, discontinue use and consult your veterinarian.
- Keep out of reach of children.

Directions

- Remove applicator cap and seal from bottle.Pour Ascorbic Acid vial contents into bottle; Replace applicator cap and wait until Ascorbic Acid reaches the bottom of bottle.Shake well to dissolve.
- Open bottle by twisting the applicator cap to expose top of tip. Apply one pea-sized back drop placed on your clean index finger, swab, or fingerbrush to the gums above back molars on both sides of the mouth for cats and small dogs.Use slighty more for medium and large dogs.
- Apply once daily or as directed by veterinarian.

Inactive Ingredients

F.D.&C. Blue No.1 (as a colorant),Methylparaben (as a preservative),Propylparaben

(as a preservative),Purified Water, Taurine, Xanthan Gum.

Preservative System

This product is preserved with Methylparaben, Propylparaben, and Zinc gluconate.

Storage

- Store unmixed product at room temperature (20-25°C/ 68-77°F)
- Store mixed product in refrigerator (2-8°C/36-46°F).A Blue or Green color denotes freshness.Replace the bottle if the color changes to yellow or brown.
- Protect from excessive heat and direct sunlight.

Addison Biological Laboratory, Inc.
507 North Cleveland Avenue
Fayette, Missouri 65248
www.addisonlabs.com
Made in the U.S.A.

Rev. 08/25